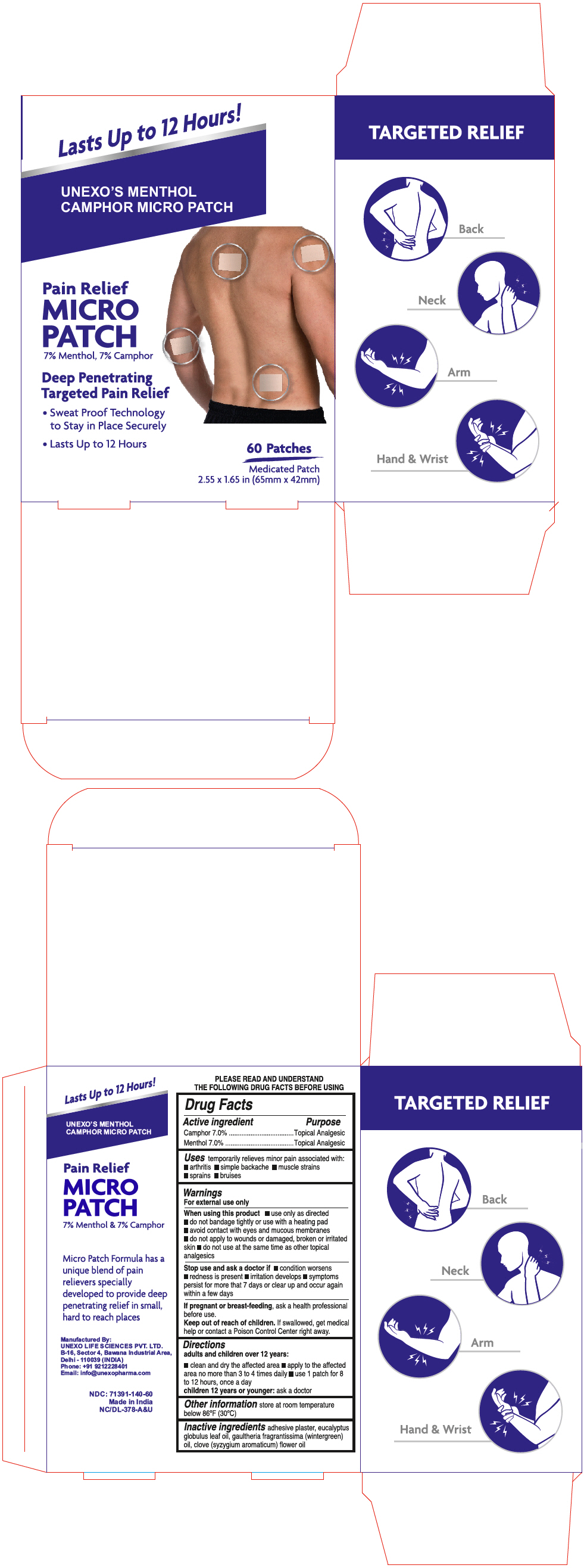 DRUG LABEL: Menthol Camphor Micro
NDC: 71391-140 | Form: PATCH
Manufacturer: Unexo Life Sciences Private Limited
Category: otc | Type: HUMAN OTC DRUG LABEL
Date: 20250113

ACTIVE INGREDIENTS: MENTHOL, UNSPECIFIED FORM 38.22 mg/1 1; CAMPHOR (NATURAL) 38.22 mg/1 1
INACTIVE INGREDIENTS: Eucalyptus oil; METHYL SALICYLATE; Clove Oil

Menthol Camphor Micro Patch

Drug Facts

ACTIVE INGREDIENT

Active ingredient | Purpose
Camphor 7.0% | Topical Analgesic
Menthol 7.0% | Topical Analgesic

Uses

temporarily relieves minor pain associated with:

- Arthritis
- Simple backache
- Muscle strains
- Sprains
- Bruises

Warnings

For external use only

When using this product

- use only as directed
- Do not bandage tightly or use with a heating pad
- Avoid contact with eyes and mucous membranes
- Do not apply to wounds or damaged, broken or irritated skin
- Do not use at the same time as other topical analgesics

Stop use and ask a doctor if

- Condition worsens
- Redness is present
- Irritation develops
- symptoms persist for more than 7 days or clear up and occur again within a few days

PREGNANCY OR BREAST FEEDING

If pregnant or breast-feeding, ask a health professional before use.

Keep out of reach of children. If swallowed, get medical help or contact a Poison Control Center right away.

Directions

Adults and children 12 years:

- clean and dry the affected area
- apply to the affected area no more than 3 to 4 times daily
- Use 1 patch for 8 to 12 hours, once per day

Children under 12 years of age:

- Ask a doctor

Other Information

- Store at room temperature below 86°F (30°C)

Inactive Ingredients

Adhesive plaster, eucalyptus globulus leaf oil, gaultheria fragrantissima (wintergreen) oil, clove (syzygium aromaticum) flower oil

Questions?

Call +91 9212228401

Manufactured By:

UNEXO LIFE SCIENCES PVT. LTD.
B-16. Sector 4, Bawana Industrial Area,
Delhi – 110039 (INDIA)

PRINCIPAL DISPLAY PANEL - 60 Patch Pouch Box

Lasts Up to 12 Hours!

UNEXO'S MENTHOL
CAMPHOR MICRO PATCH

Pain Relief
MICRO
PATCH
7% Menthol, 7% Camphor

Deep Penetrating
Targeted Pain Relief

- Sweat Proof Technology
  to Stay in Place Securely
- Lasts Up to 12 Hours

60 Patches

Medicated Patch
2.55 x 1.65 in (65mm x 42mm)